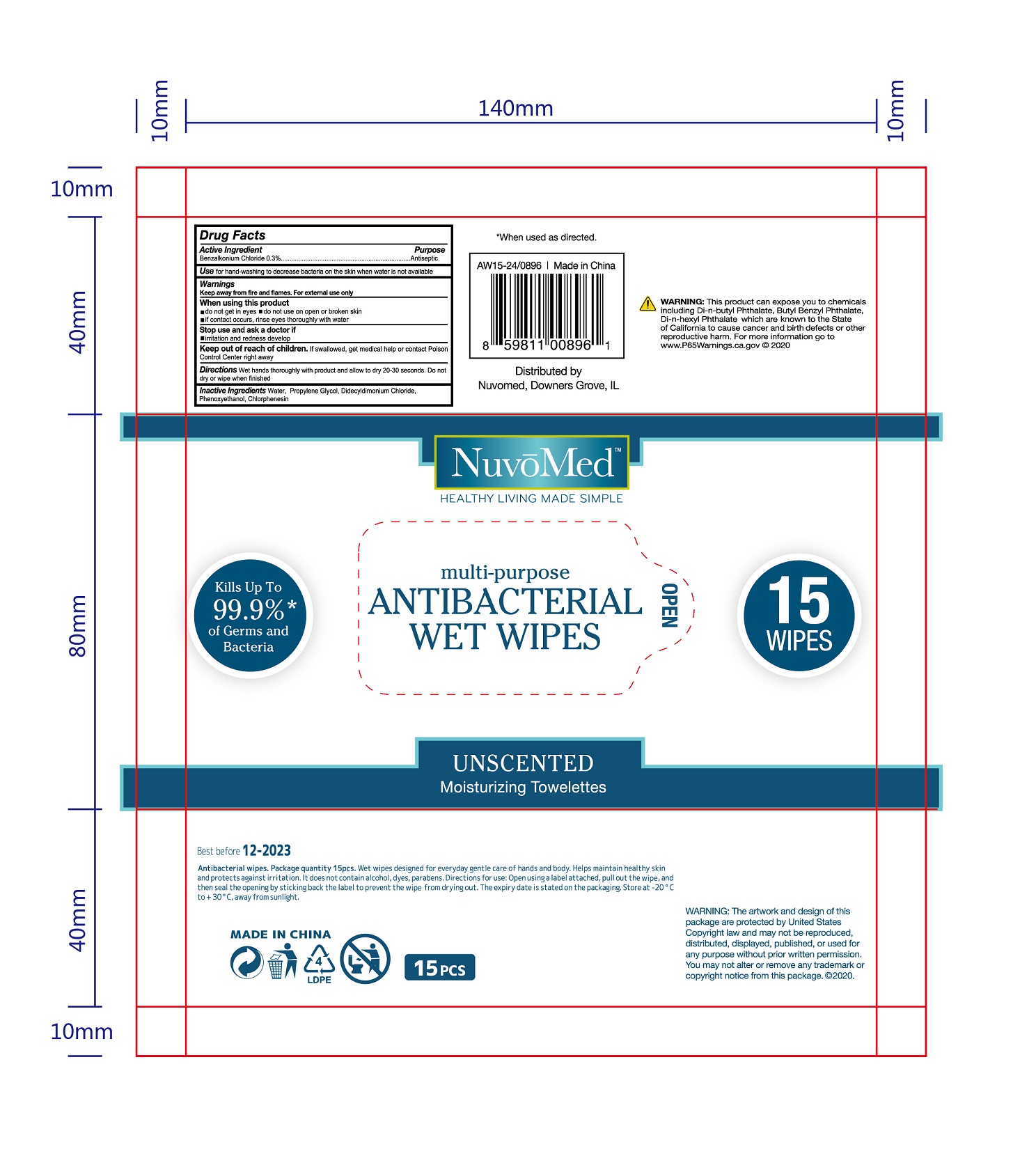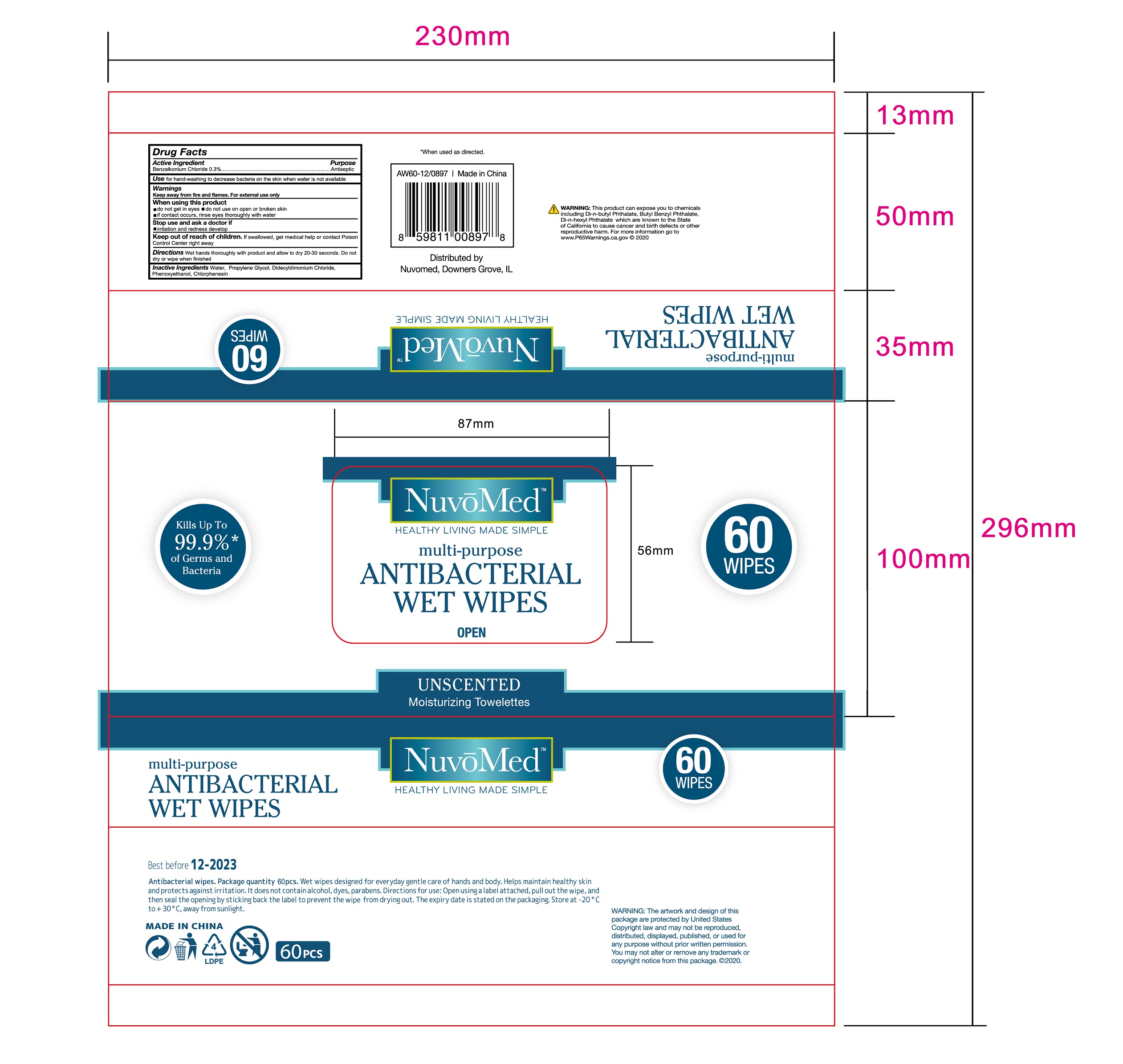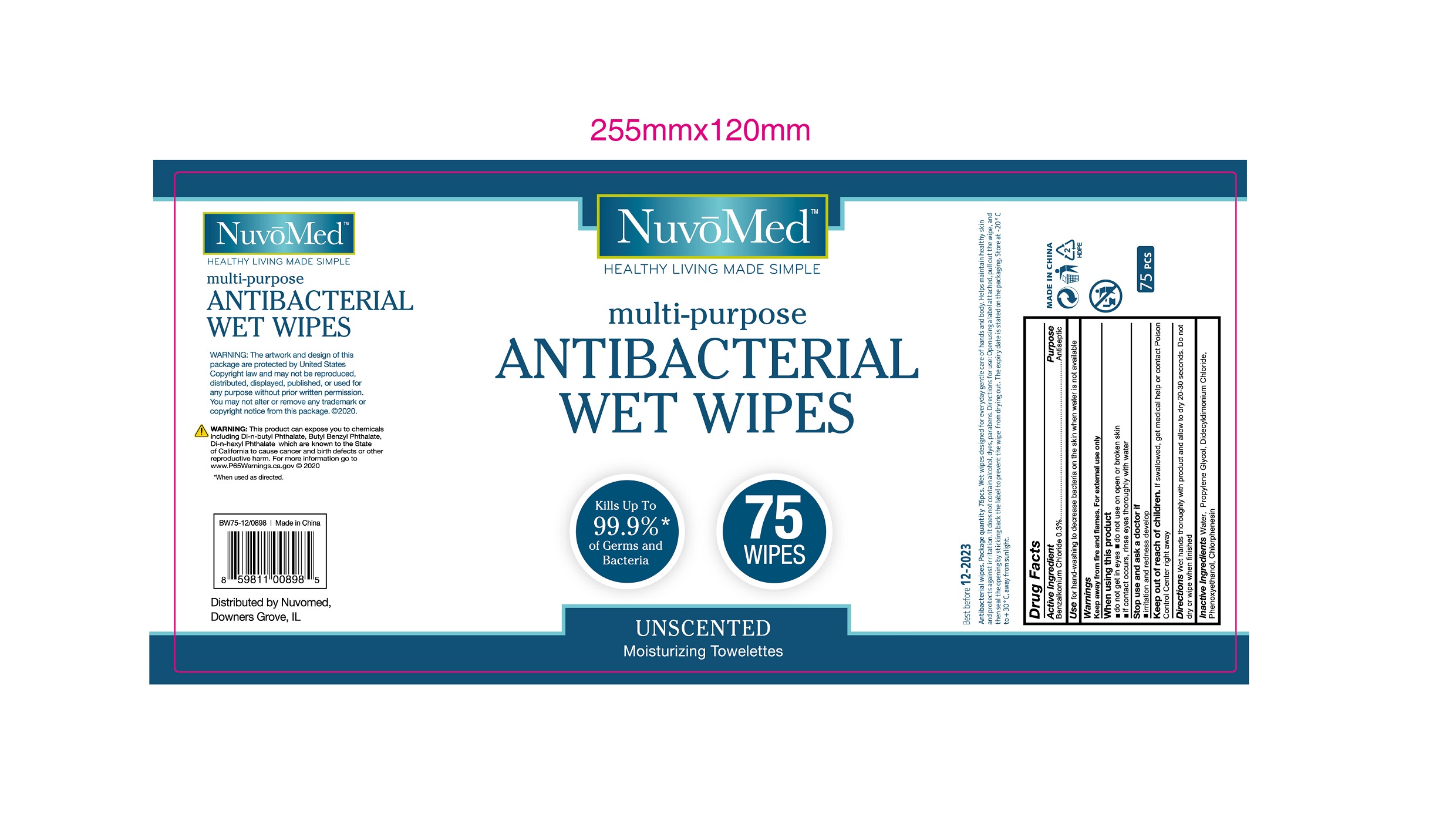 DRUG LABEL: NUVOMED Antibacterial Wet Wipes
NDC: 76635-005 | Form: CLOTH
Manufacturer: Hangzhou Glamcos Biotech CO.,LTD
Category: otc | Type: HUMAN OTC DRUG LABEL
Date: 20231123

ACTIVE INGREDIENTS: BENZALKONIUM CHLORIDE 0.3 g/100 g
INACTIVE INGREDIENTS: PROPYLENE GLYCOL; PHENOXYETHANOL; DIDECYLDIMONIUM CHLORIDE; WATER; CHLORPHENESIN

Drug Facts

Active Ingredient(s)

Benzalkonium Chloride 0.3%

Purpose

Antiseptic

Use

Use for hand-washing to decrease bacteria on the skin when water is not available.

Warnings

Keep away from fire and flames.For external use only.

Do not use on open or broken skin.If contact occurs,rinse eyes thoroughly with water.

When using this product ,do not get in eyes.

Stop use and ask a doctor if irritation and redness develop.

Keep out of reach of children.If swallowed,get medical help or contact poison control center right away.

Directions

Wet hands thoroughly with product and allow to dry 20-30 seconds.Do not dry or wipe when finished.

Other information

The espiry date is stated on the packaging.Store at -20℃ to+30℃,away from sunlight.

Inactive ingredients

Water，Propylene Glycol，DidecyldimoniumChloride ，Phenoxyethanol， Chlorphenesin.